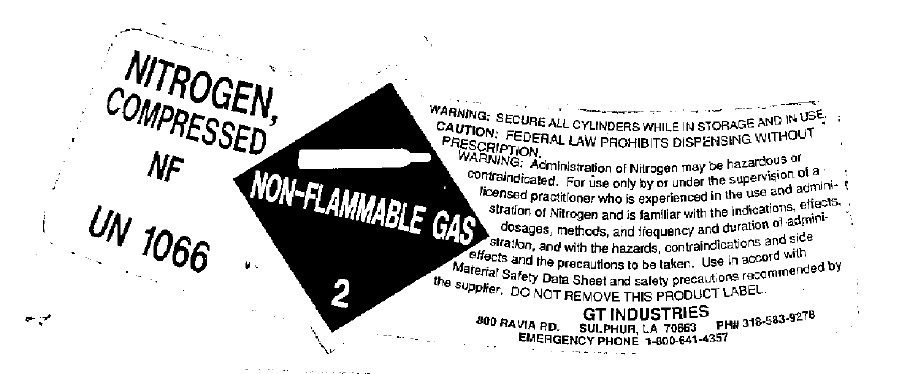 DRUG LABEL: Nitrogen
NDC: 61095-200 | Form: GAS
Manufacturer: GT Industries Inc
Category: prescription | Type: HUMAN PRESCRIPTION DRUG LABEL
Date: 20100525

ACTIVE INGREDIENTS: Nitrogen 990 mL/1 L

nitrogen

PACKAGE LABEL

NITROGEN, COMPRESSED NF UN1066
NON-FLAMMABLE GAS 2
WARNING: SECURE ALL CYLINDERS WHILE IN STORAGE AND IN USE. CAUTION: FEDERAL LAW PROHIBITS DISPENSING WITHOUT PRESCRIPTION. WARNING: Administration of Nitrogen may be hazardous or contraindicated. For use only by or under the supervision of a licensed practitioner who is experienced in the use and administration of Nitrogen, and is familiar with the indications, effects, dosages, methods, and frequency and duration of administration, and with the hazards, contraindications, and side effects, and the precautions to be taken. . Use in accordance with the Material Safety Data Sheet and the precautions recommended by the supplier. DO NOT REMOVE THIS PRODUCT LABEL. GT INDUSTRIES 800 RAVIA RD. SULPHUR, LA 70663 PH# 318-583-9278 EMERGENCY PHONE 1-800-641-4357